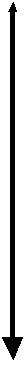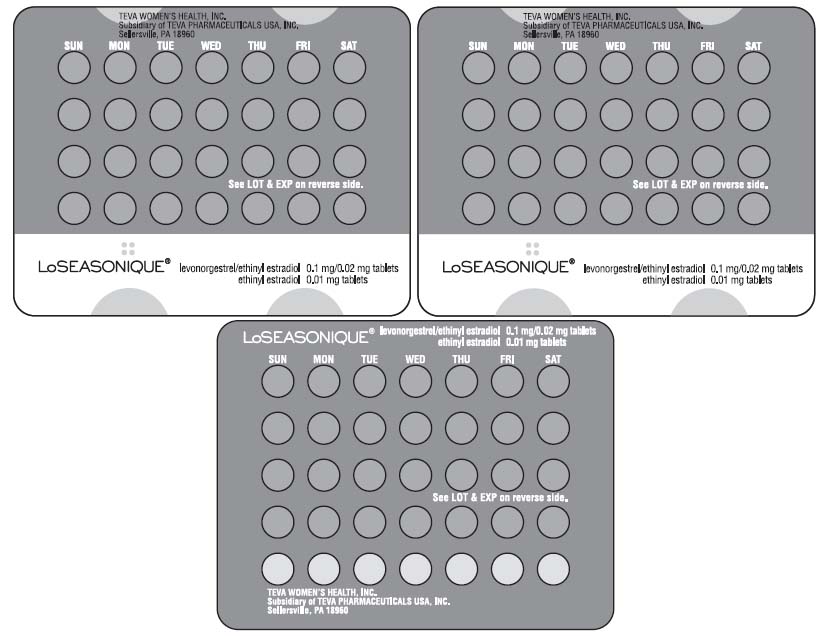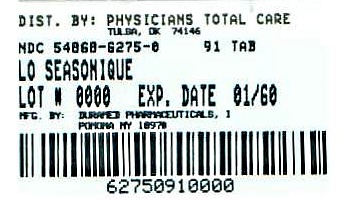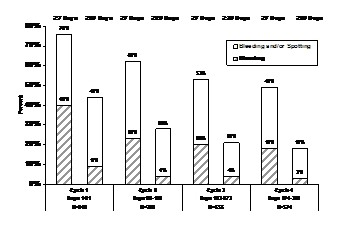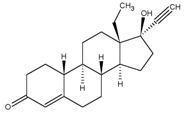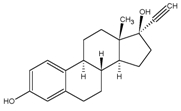 DRUG LABEL: LoSeasonique
NDC: 54868-6275 | Form: KIT | Route: ORAL
Manufacturer: Physicians Total Care, Inc.
Category: prescription | Type: HUMAN PRESCRIPTION DRUG LABEL
Date: 20120110

ACTIVE INGREDIENTS: LEVONORGESTREL 0.1 mg/1 1; ETHINYL ESTRADIOL 0.02 mg/1 1; ETHINYL ESTRADIOL 0.01 mg/1 1
INACTIVE INGREDIENTS: STARCH, CORN; FD&C YELLOW NO. 6; HYPROMELLOSES; LACTOSE; MAGNESIUM STEARATE; CELLULOSE, MICROCRYSTALLINE; TITANIUM DIOXIDE; TRIACETIN; ANHYDROUS LACTOSE; D&C YELLOW NO. 10; FD&C YELLOW NO. 6; HYPROMELLOSES; MAGNESIUM STEARATE; CELLULOSE, MICROCRYSTALLINE; POLACRILIN POTASSIUM; POLYETHYLENE GLYCOL; POLYSORBATE 80; TITANIUM DIOXIDE

HIGHLIGHTS OF PRESCRIBING INFORMATION

These highlights do not include all the information needed to use LoSeasonique tablets safely and effectively. See full prescribing information for LoSeasonique.
LoSeasonique (levonorgestrel/ethinyl estradiol tablets and ethinyl estradiol tablets) for oral use
Initial U.S. Approval: 1982

WARNING: CIGARETTE SMOKING AND SERIOUS CARDIOVASCULAR EVENTS

See full prescribing information for complete boxed warning

- Women who are over 35 years old and smoke should not use LoSeasonique. (4)
- Cigarette smoking increases the risk of serious cardiovascular events from combination oral contraceptive (COC) use.

1 INDICATIONS AND USAGE

LoSeasonique is an estrogen/progestin COC indicated for use by women to prevent pregnancy. (1)

2 DOSAGE AND ADMINISTRATION

Take one tablet daily by mouth at the same time every day for 91 days. (2)

3 DOSAGE FORMS AND STRENGTHS

LoSeasonique consists of 84 orange tablets containing 0.1 mg levonorgestrel and 0.02 mg ethinyl estradiol, and 7 yellow tablets containing 0.01 mg ethinyl estradiol. (3)

4 CONTRAINDICATIONS

- A high risk of arterial or venous thrombotic diseases (4)
- Breast cancer or other estrogen- or progestin-sensitive cancer (4)
- Liver tumors or liver disease (4)
- Pregnancy (4)

5 WARNINGS AND PRECAUTIONS

- Vascular risks: Stop LoSeasonique if a thrombotic event occurs. Stop LoSeasonique at least 4 weeks before and through 2 weeks after major surgery. Start LoSeasonique no earlier than 4 weeks after delivery, in women who are not breastfeeding. (5.1)
- Liver disease: Discontinue LoSeasonique if jaundice occurs. (5.3)
- High blood pressure: Do not prescribe LoSeasonique for women with uncontrolled hypertension or hypertension with vascular disease. (5.4)
- Carbohydrate and lipid metabolic effects: Monitor prediabetic and diabetic women taking LoSeasonique. Consider an alternate contraceptive method for women with uncontrolled dyslipidemias. (5.6)
- Headache: Evaluate significant change in headaches and discontinue LoSeasonique if indicated. (5.7)
- Uterine bleeding: Evaluate irregular bleeding or amenorrhea. (5.8)

6 ADVERSE REACTIONS

The most common adverse reactions for COCs are irregular uterine bleeding, nausea, breast tenderness, and headaches. (6)

To report SUSPECTED ADVERSE REACTIONS, contact Teva Women’s Health at 1-800-222-0190 or FDA at 1-800-FDA-1088 or www.fda.gov/medwatch

7 DRUG INTERACTIONS

Drugs or herbal products that induce certain enzymes, including CYP3A4, may decrease the effectiveness of COCs or increase breakthrough bleeding. Counsel patients to use a back-up method or alternative method of contraception when enzyme inducers are used with COCs. (7)

8 USE IN SPECIFIC POPULATIONS

- Nursing: Not recommended for nursing mothers; can decrease milk production (8.3)

FULL PRESCRIBING INFORMATION

WARNING: CIGARETTE SMOKING AND SERIOUS CARDIOVASCULAR EVENTS

Cigarette smoking increases the risk of serious cardiovascular events from combination oral contraceptives (COC) use. This risk increases with age, particularly in women over 35 years of age, and with the number of cigarettes smoked. For this reason, COCs should not be used by women who are over 35 years of age and smoke. [See CONTRAINDICATIONS (4).]

1 INDICATIONS AND USAGE

LoSeasonique (levonorgestrel/ethinyl estradiol tablets and ethinyl estradiol tablets) is indicated for use by women to prevent pregnancy.

2 DOSAGE AND ADMINISTRATION

Take one tablet by mouth at the same time every day. The dosage of LoSeasonique is one orange tablet containing levonorgestrel and ethinyl estradiol daily for 84 consecutive days, followed by one yellow ethinyl estradiol tablet for 7 days. To achieve maximum contraceptive effectiveness, LoSeasonique must be taken exactly as directed and at intervals not exceeding 24 hours.

Instruct the patient to begin taking LoSeasonique on the first Sunday after the onset of menstruation. If menstruation begins on a Sunday, the first orange tablet is taken that day. One orange tablet should be taken daily for 84 consecutive days, followed by one yellow tablet for 7 consecutive days. A non-hormonal back-up method of contraception (such as condoms or spermicide) should be used until an orange tablet has been taken daily for 7 consecutive days. A scheduled period should occur during the 7 days that the yellow tablets are taken.

Begin the next and all subsequent 91-day cycles without interruption on the same day of the week (Sunday) on which the patient began her first dose of LoSeasonique, following the same schedule: 84 days taking an orange tablet followed by 7 days taking a yellow tablet. If the patient does not immediately start her next pill pack, she should protect herself from pregnancy by using a non-hormonal back-up method of contraception until she has taken an orange tablet daily for 7 consecutive days.

If unscheduled spotting or bleeding occurs, instruct the patient to continue on the same regimen. If the bleeding is persistent or prolonged, advise the patient to consult her healthcare provider.

For patient instructions regarding missed pills, see PATIENT COUNSELING INFORMATION (17.2).

For postpartum women who are not breastfeeding, start LoSeasonique no earlier than four to six weeks postpartum. If the patient starts on LoSeasonique postpartum and has not yet had a period, evaluate for possible pregnancy, and instruct her to use an additional method of contraception until she has taken an orange tablet for 7 consecutive days.

3 DOSAGE FORMS AND STRENGTHS

LoSeasonique tablets are available in Extended-Cycle Tablet Dispensers, each containing a 13-week supply of tablets: 84 orange tablets, each containing 0.1 mg of levonorgestrel and 0.02 mg ethinyl estradiol, and 7 yellow tablets each containing 0.01 mg of ethinyl estradiol. The orange tablets are round, film-coated, unscored tablets with a debossed stylized b on one side and 28 on the other side. The yellow tablets are round, film-coated, unscored tablet with a debossed stylized b on one side and 556 on the other side.

4 CONTRAINDICATIONS

Do not prescribe LoSeasonique to women who are known to have the following conditions:

- A high risk of arterial or venous thrombotic diseases. Examples include women who are known to:
  - Smoke, if over age 35
  - Have deep vein thrombosis or pulmonary embolism, now or in the past
  - Have cerebrovascular disease
  - Have coronary artery disease
  - Have thrombogenic valvular or thrombogenic rhythm diseases of the heart (for example, subacute bacterial endocarditis with valvular disease, or atrial fibrillation)
  - Have hypercoagulopathies
  - Have uncontrolled hypertension
  - Have diabetes with vascular disease
  - Have headaches with focal neurological symptoms or have migraine headaches with or without aura if over age 35
- Breast cancer or other estrogen- or progestin-sensitive cancer, now or in the past
- Liver tumors, benign or malignant, or liver disease
- Pregnancy, because there is no reason to use OCs during pregnancy

5 WARNINGS AND PRECAUTIONS

5.1 Vascular Events

Stop COCs if an arterial or deep venous thrombotic event occurs. Although use of COCs increases the risk of venous thromboembolism, pregnancy increases the risk of venous thromboembolism as much or more than the use of COCs. The risk of venous thromboembolism in women using COCs is 3 to 9 per 10,000 woman-years. Use of COCs also increases the risk of arterial thromboses such as strokes and myocardial infarctions, especially in women with other risk factors for these events.

Use of LoSeasonique provides women with more hormonal exposure on a yearly basis than conventional monthly oral contraceptives containing the same strength synthetic estrogens and progestins (an additional 9 and 13 weeks of exposure to progestin and estrogen, respectively, per year.)

If feasible, stop COCs at least 4 weeks before and through 2 weeks after major surgery or other surgeries known to have an elevated risk of thromboembolism.

Start COCs no earlier than 4 weeks after delivery, in women who are not breastfeeding. The risk of postpartum thromboembolism decreases after the third postpartum week, whereas the risk of ovulation increases after the third postpartum week.

Stop COCs if there is unexplained loss of vision, proptosis, diplopia, papilledema, or retinal vascular lesions. Evaluate for retinal vein thrombosis immediately.

5.2 Carcinoma of the Breast and Cervix

Women who currently have or have had breast cancer should not use COCs because breast cancer may be hormonally sensitive.

There is substantial evidence that COCs do not increase the incidence of breast cancer. Although some past studies have suggested that COCs might increase the incidence of breast cancer, more recent studies have not confirmed such findings.

Some studies suggest that COCs are associated with an increase in the risk of cervical cancer or intraepithelial neoplasia. However, there is controversy about the extent to which these findings are due to differences in sexual behavior and other factors.

5.3 Liver Disease

Discontinue COCs if jaundice develops. Steroid hormones may be poorly metabolized in patients with impaired liver function.

Hepatic adenomas are associated with COC use. An estimate of the attributable risk is 3.3 cases/100,000 COC users. Rupture of hepatic adenomas may cause death through intra-abdominal hemorrhage.

Studies have shown an increased risk of developing hepatocellular carcinoma in long-term (> 8 years) COC users. However, the attributable risk of liver cancers in COC users is less than one case per million users.

Oral contraceptive-related cholestasis may occur in women with a history of pregnancy-related cholestasis. Women with a history of COC-related cholestasis may have the condition recur with subsequent COC use.

5.4 High Blood Pressure

For women with well-controlled hypertension, monitor blood pressure and stop COCs if blood pressure rises significantly. Women with uncontrolled hypertension or hypertension with vascular disease should not use COCs.

An increase in blood pressure has been reported in women taking COCs, and this increase is more likely in older women and with extended duration of use. The incidence of hypertension increases with increasing concentration of progestin.

5.5 Gallbladder Disease

Studies suggest a small increased relative risk of developing gallbladder disease among COC users.

5.6 Carbohydrate and Lipid Metabolic Effects

Carefully monitor prediabetic and diabetic women who are taking COCs. COCs may decrease glucose tolerance in a dose-related fashion.

Consider alternative contraception for women with uncontrolled dyslipidemias. A small proportion of women will have adverse lipid changes while on COCs.

5.7 Headache

If a woman taking COCs develops new headaches that are recurrent, persistent, or severe, evaluate the cause and discontinue COCs if indicated.

5.8 Bleeding Irregularities

Unscheduled (breakthrough) bleeding and spotting sometimes occur in patients on COCs, especially during the first 3 months of use. If bleeding persists, check for causes such as pregnancy or malignancy. If pathology and pregnancy are excluded, bleeding irregularities may resolve over time or with a change to a different COC product.

When prescribing LoSeasonique, the convenience of fewer planned menses (4 per year instead of 13 per year) should be weighed against the inconvenience of increased unscheduled bleeding and/or spotting. The clinical trial that evaluated the efficacy of LoSeasonique also assessed unscheduled bleeding. The participants in this 12-month clinical trial (N=2,185) completed the equivalent of over 20,000 28-day cycles of exposure and were composed primarily of women who had used OCs previously (89%), as opposed to new users (11%). A total of 209 subjects (9.6%) discontinued LoSeasonique, at least in part, due to bleeding and/or spotting.

Scheduled (withdrawal) bleeding and/or spotting remained fairly constant over time, with an average of 2-3 days of bleeding and/or spotting per each 91-day cycle. Unscheduled bleeding and unscheduled spotting decreased over successive 91-day cycles. Table 1 below presents the number of days with unscheduled bleeding in treatment cycles 1 and 4. Table 2 presents the number of days with unscheduled spotting in treatment cycles 1 and 4.

Table 1: Total Number of Days with Unscheduled Bleeding
91-Day Treatment Cycle | Days per 84-Day Interval |  |  |  | Days per 28-Day Interval
91-Day Treatment Cycle | Q1 | Median | Q3 | Mean | Mean
1st | 0 | 5 | 11 | 7.5 | 2.5
4th | 0 | 0 | 5 | 3.5 | 1.2

Q1=Quartile 1: 25% of women had this number of days of unscheduled bleeding

Median: 50% of women had ≤ this number of days of unscheduled bleeding

Q3=Quartile 3: 75% of women had ≤ this number of days of unscheduled bleeding

Table 2: Total Number of Days with Unscheduled Spotting
91-Day Treatment Cycle | Days per 84-Day Interval |  |  |  | Days per 28-Day Interval
91-Day Treatment Cycle | Q1 | Median | Q3 | Mean | Mean
1st | 3 | 10 | 19 | 14.0 | 4.7
4th | 0 | 3 | 10 | 6.5 | 2.2

Q1=Quartile 1: 25% of women had ≤ this number of days of unscheduled spotting

Median: 50% of women had ≤ this number of days of unscheduled spotting

Q3=Quartile 3: 75% of women had ≤ this number of days of unscheduled spotting

Figure 1 shows the percentage of LoSeasonique subjects participating in the primary clinical trial with ≥ 7 days or ≥ 20 days of unscheduled bleeding and/or spotting, or just unscheduled bleeding, during each 91-day treatment cycle.

Figure 1. Percent of Women Taking LoSeasonique who Reported Unscheduled Bleeding and/or Spotting (Based on Daily Diaries)

Amenorrhea sometimes occurs in women who are using COCs. Pregnancy should be ruled out in the event of amenorrhea. Some women may encounter amenorrhea or oligomenorrhea after stopping COCs, especially when such a condition was pre-existent.

5.9 Interference with Laboratory Tests

The use of COCs may change the results of some laboratory tests, such as coagulation factors, lipids, glucose tolerance, and binding proteins. Women on thyroid hormone replacement therapy may need increased doses of thyroid hormone because serum concentrations of thyroid binding globulin increase with use of COCs.

5.10 Monitoring

A woman who is taking COCs should have a yearly visit with her healthcare provider for a blood pressure check and for other indicated healthcare.

6 ADVERSE REACTIONS

The following serious adverse reactions with the use of COCs are discussed elsewhere in the labeling:

- Serious cardiovascular events and smoking [see BOXED WARNING]
- Vascular events [see WARNINGS AND PRECAUTIONS (5.1)]
- Liver disease [see WARNINGS AND PRECAUTIONS (5.3)]

Adverse reactions commonly reported by COC users are:

- Irregular uterine bleeding
- Nausea
- Breast tenderness
- Headache

6.1 Clinical Trial Experience

Because clinical trials are conducted under widely varying conditions, adverse reaction rates observed in the clinical trials of a drug cannot be directly compared to the rates in the clinical trials of another drug and may not reflect the rates observed in practice.

The clinical trial that evaluated the safety and efficacy of LoSeasonique was a 12-month, multicenter, non-comparative open-label study, which enrolled women aged 18-41, of whom 2,185 took at least one dose of LoSeasonique.

Adverse Reactions Leading to Study Discontinuation: 11% of the women discontinued from the clinical trial due to an adverse reaction; the most common adverse reactions leading to discontinuation were irregular and/or heavy uterine bleeding, headache, mood changes, nausea, acne, and weight gain.

Common Treatment-Emergent Adverse Reactions (≥ 5% of women): headaches (33%); irregular and/or heavy uterine bleeding (13%), dysmenorrhea (11%), nausea and/or vomiting (11%), back pain (8%).

7 DRUG INTERACTIONS

No formal drug-drug interaction studies were conducted with LoSeasonique.

7.1 Changes in Contraceptive Effectiveness Associated with Co-Administration of Other Products

If a woman on hormonal contraceptives takes a drug or herbal product that induces enzymes, including CYP3A4, that metabolize contraceptive hormones, counsel her to use additional contraception or a different method of contraception. Drugs or herbal products that induce such enzymes may decrease the plasma concentrations of contraceptive hormones, and may decrease the effectiveness of hormonal contraceptives or increase breakthrough bleeding. Some drugs or herbal products that may decrease the effectiveness of hormonal contraceptives include:

- barbiturates
- bosentan
- carbamazepine
- felbamate
- griseofulvin
- oxcarbazepine
- phenytoin
- rifampin
- St. John’s wort
- topiramate

HIV protease inhibitors: Significant changes (increase or decrease) in the plasma levels of the estrogen and progestin have been noted in some cases of co-administration of HIV protease inhibitors.

Antibiotics: There have been reports of pregnancy while taking hormonal contraceptives and antibiotics, but clinical pharmacokinetic studies have not shown consistent effects of antibiotics on plasma concentrations of synthetic steroids.

Consult the labeling of all concurrently-used drugs to obtain further information about interactions with hormonal contraceptives or the potential for enzyme alterations.

7.2 Increase in Plasma Levels of Estradiol Associated with Co-Administered Drugs

Co-administration of atorvastatin and certain COCs containing ethinyl estradiol increase AUC values for ethinyl estradiol by approximately 20%. Ascorbic acid and acetaminophen may increase plasma ethinyl estradiol levels, possibly by inhibition of conjugation. CYP3A4 inhibitors such as itraconazole or ketoconazole may increase plasma hormone levels.

7.3 Changes in Plasma Levels of Co-Administered Drugs

Combination OCs containing some synthetic estrogens (e.g., ethinyl estradiol) may inhibit the metabolism of other compounds. Combination OCs have been shown to significantly decrease plasma concentrations of lamotrigine likely due to induction of lamotrigine glucuronidation. This may reduce seizure control; therefore, dosage adjustments of lamotrigine may be necessary. Consult the labeling of the concurrently-used drug to obtain further information about interactions with COCs or the potential for enzyme alterations.

8 USE IN SPECIFIC POPULATIONS

8.1 Pregnancy

There is little or no increased risk of birth defects in women who inadvertently use COCs during early pregnancy. Epidemiologic studies and meta-analyses have not found an increased risk of genital or non-genital birth defects (including cardiac anomalies and limb reduction defects) following exposure to low dose COCs prior to conception or during early pregnancy.

The administration of COCs to induce withdrawal bleeding should not be used as a test for pregnancy. Combination OCs should not be used during pregnancy to treat threatened or habitual abortion.

Women who do not breastfeed may start COCs no earlier than four to six weeks postpartum.

8.3 Nursing Mothers

When possible, advise the nursing mother to use other forms of contraception until she has weaned her child. Estrogen-containing OCs can reduce milk production in breastfeeding mothers. This is less likely to occur once breastfeeding is well established; however, it can occur at any time in some women. Small amounts of estrogen and progestin from low dose COCs are present in breast milk, but these doses have not produced adverse effects in breastfeeding infants.

8.4 Pediatric Use

Safety and efficacy of LoSeasonique have been established in women of reproductive age. Safety and efficacy are expected to be the same for postpubertal adolescents under the age of 18 as for users 18 years and older. Use of this product before menarche is not indicated.

8.5 Geriatric Use

This product has not been studied in postmenopausal women and is not indicated in this population.

10 OVERDOSAGE

There have been no reports of serious ill effects from overdose, including ingestion by children. Overdosage may cause withdrawal bleeding in females and nausea.

11 DESCRIPTION

LoSeasonique (levonorgestrel/ethinyl estradiol and ethinyl estradiol) tablets provide an oral contraceptive regimen of 84 orange tablets each containing 0.1 mg levonorgestrel and 0.02 mg ethinyl estradiol, followed by 7 yellow tablets each containing 0.01 mg ethinyl estradiol.

The structural formulas for the active components are:

Levonorgestrel C21H28O2 MW: 312.4

Levonorgestrel is chemically 18,19-Dinorpregn-4-en-20-yn-3-one, 13-ethyl-17-hydroxy-, (17α)-, (-)-.

Ethinyl Estradiol C20H24O2 MW: 296.4

Ethinyl Estradiol is 19-Norpregna-1,3,5(10)-trien-20-yne-3,17-diol, (17α)-.

Inactive ingredients for the orange tablets include FD&C Yellow # 6 (Sunset Yellow) aluminum lake, hypromellose, lactose, magnesium stearate, microcrystalline cellulose, corn starch, titanium dioxide and triacetin.

Inactive ingredients for the yellow tablets include anhydrous lactose, FD&C Yellow # 10 aluminum lake, FD&C Yellow # 6 (Sunset Yellow) aluminum lake, hypromellose, magnesium stearate, microcrystalline cellulose, polacrilin potassium, polyethylene glycol, polysorbate 80 and titanium dioxide.

12 CLINICAL PHARMACOLOGY

12.1 Mechanism of Action

Combination OCs lower the risk of becoming pregnant primarily by suppressing ovulation. Other possible mechanisms may include cervical mucus changes that inhibit sperm penetration and endometrial changes that reduce the likelihood of implantation.

12.3 Pharmacokinetics

Absorption

No specific investigation of the absolute bioavailability of LoSeasonique in humans has been conducted. However, literature indicates that levonorgestrel is rapidly and completely absorbed after oral administration (bioavailability nearly 100%) and is not subject to first-pass metabolism. Ethinyl estradiol is rapidly and almost completely absorbed from the gastrointestinal tract but, due to first-pass metabolism in gut mucosa and liver, the systemic bioavailability of ethinyl estradiol is approximately 43%.

The mean plasma pharmacokinetic parameters of LoSeasonique following a single oral dose of three levonorgestrel/ethinyl estradiol combination tablets in normal healthy women under fasting conditions are reported in Table 3.

Table 3: Mean (SD) Pharmacokinetic Parameters Following a Single Dose Administration of Three Tablets of LoSeasonique in 30 Healthy Women under Fasting Conditions
 | AUC0-∞ | Cmax | Tmax | T½
Levonorgestrel | 76.5 ± 24.9 ng*hr/mL | 6.0 ± 1.6 ng/mL | 1.6 ± 0.6 hours | 28.5 ± 8.7 hours
Ethinyl estradiol | 1335.8 ± 365.3 pg*hr/mL | 122.8 ± 39.5 pg/mL | 1.8 ± 0.7 hours | 17.5 ± 7.4 hours

AUC0-∞ = area under the drug concentration curve from time 0 to infinity

Cmax = maximum concentration

Tmax = time to maximum concentration

The effect of food on the rate and the extent of levonorgestrel and ethinyl estradiol absorption following oral administration of LoSeasonique has not been evaluated.

Distribution

The apparent volume of distribution of levonorgestrel and ethinyl estradiol is reported to be approximately 1.8 L/kg and 4.3 L/kg, respectively. Levonorgestrel is about 97.5 to 99% protein-bound, principally to sex hormone binding globulin (SHBG) and, to a lesser extent, serum albumin. Ethinyl estradiol is about 95 to 97% bound to serum albumin. Ethinyl estradiol does not bind to SHBG, but induces SHBG synthesis, which leads to decreased levonorgestrel clearance. Following repeated daily dosing of combination levonorgestrel/ethinyl estradiol OCs, levonorgestrel plasma concentrations accumulate more than predicted based on single-dose pharmacokinetics, due in part, to increased SHBG levels that are induced by ethinyl estradiol, and a possible reduction in hepatic metabolic capacity.

Metabolism

Following absorption, levonorgestrel is conjugated at the 17β-OH position to form sulfate conjugates and, to a lesser extent, glucuronide conjugates in plasma. Significant amounts of conjugated and unconjugated 3α, 5β-tetrahydrolevonorgestrel are also present in plasma, along with much smaller amounts of 3α, 5α-tetrahydrolevonorgestrel and 16β-hydroxylevonorgestrel. Levonorgestrel and its phase I metabolites are excreted primarily as glucuronide conjugates. Metabolic clearance rates may differ among individuals by several-fold, and this may account in part for the wide variation observed in levonorgestrel concentrations among users.

First-pass metabolism of ethinyl estradiol involves formation of ethinyl estradiol-3-sulfate in the gut wall, followed by 2-hydroxylation of a portion of the remaining untransformed ethinyl estradiol by hepatic cytochrome P-450 3A4 (CYP3A4). Levels of CYP3A4 vary widely among individuals and can explain the variation in rates of ethinyl estradiol hydroxylation. Hydroxylation at the 4-, 6-, and 16- positions may also occur, although to a much lesser extent than 2-hydroxylation. The various hydroxylated metabolites are subject to further methylation and/or conjugation.

Excretion

About 45% of levonorgestrel and its metabolites are excreted in the urine and about 32% are excreted in feces, mostly as glucuronide conjugates. Ethinyl estradiol is excreted in the urine and feces as glucuronide and sulfate conjugates, and then undergoes enterohepatic recirculation.

Race

The effect of race on the pharmacokinetics of LoSeasonique has not been evaluated.

Renal and Hepatic Impairment

No formal studies were conducted to evaluate the effect of hepatic or renal disease on the disposition of LoSeasonique. However, steroid hormones may be poorly metabolized in patients with impaired liver function.

13 NONCLINICAL TOXICOLOGY

13.1 Carcinogenesis, Mutagenesis, Impairment of Fertility

[See WARNINGS AND PRECAUTIONS (5.2, 5.3).]

14 CLINICAL STUDIES

In a 12-month multicenter open-label clinical trial, 2,185 women aged 18-41 were studied to assess the safety and efficacy of LoSeasonique, completing the equivalent of 20,937 28-day cycles of exposure. The racial demographic of those enrolled was: Caucasian (75%), African-American (12%), Hispanic (10%), Asian (2%), and Other (2%). There were no exclusions for body mass index (BMI) or weight. The weight range for those women treated was 87 to 381 lbs., with a mean weight of 159 lbs. Among the women in the trial, 59% were current or recent hormonal contraceptive users, 30% were prior users (had used hormonal contraceptives in the past but not in the 6 months prior to enrollment) and 11% were new starts. Of treated women, 14.2% were lost to follow-up, 11.6% discontinued due to an adverse event, and 10.3% discontinued by withdrawing their consent.

The pregnancy rate (Pearl Index [PI]) in women aged 18 to 35 years was 2.74 pregnancies per 100 women-years of use (95% confidence interval 1.92 – 3.78), based on 36 pregnancies that occurred after the onset of treatment and within 14 days after the last combination pill. Cycles in which conception did not occur, but which included the use of backup contraception, were not included in the calculation of the PI. The PI includes patients who did not take the drug correctly.

16 HOW SUPPLIED/STORAGE AND HANDLING

Lo Seasonique (levonorgestrel/ethinyl estradiol tablets and ethinyl estradiol tablets) are available in an Extended-Cycle Tablet Dispenser that contains 84 round, orange tablets and 7 round, yellow tablets. Each orange tablet (debossed stylized b on one side and 28 on the other side) contains 0.1 mg levonorgestrel and 0.02 mg ethinyl estradiol. Each yellow tablet (debossed stylized b on one side and 556 on the other side) contains 0.01 mg ethinyl estradiol. The tablets should not be removed from the protective blister packaging and outer plastic dispenser to avoid damage to the product. The plastic dispenser should be kept in the foil pouch until dispensed to the patient.

Box of 1 Extended-Cycle Tablet Dispensers NDC 54868-6275-0

Storage

Store at 20 to 25°C (68 to77°F) [See USP Controlled Room Temperature].

17 PATIENT COUNSELING INFORMATION

See FDA-APPROVED PATIENT LABELING (17.2)

17.1 Information for Patients

- Counsel patients that cigarette smoking increases the risk of serious cardiovascular events from COC use, and that women who are over 35 years old and smoke should not use COCs.
- Counsel patients that this product does not protect against HIV-infection (AIDS) and other sexually transmitted diseases.
- Counsel patients to take one tablet daily by mouth at the same time every day. Instruct patients what to do in the event pills are missed.
- Counsel patients to use a back-up or alternative method of contraception when enzyme inducers are used with COCs.
- Counsel patients who are breastfeeding or who desire to breastfeed that COCs may reduce breast milk production. This is less likely to occur if breastfeeding is well established.
- Counsel any patient who starts COCs postpartum, and who has not yet had a period, to use an additional method of contraception until she has taken an orange tablet for 7 consecutive days.

PATIENT INFORMATION

Guide for Using LoSeasonique

WARNING TO WOMEN WHO SMOKE

Do not use LoSeasonique if you smoke cigarettes and are over 35 years old. Smoking increases your risk of serious cardiovascular side effects from birth control pills, including death from heart attack, blood clots or stroke. This risk increases with age and the number of cigarettes you smoke.

Birth control pills help to lower the chances of becoming pregnant. They do not protect against HIV infection (AIDS) and other sexually transmitted diseases.

WHAT IS LoSeasonique?

LoSeasonique is a birth control pill. It contains two female hormones, an estrogen called ethinyl estradiol, and a progestin called levonorgestrel.

HOW WELL DOES LoSeasonique WORK?

Your chance of getting pregnant depends on how well you follow the directions for taking your birth control pills. The more carefully you follow the directions, the less chance you have of getting pregnant.

Based on the results of a single clinical study lasting 12 months, 2 to 4 women, out of 100 women, may get pregnant during the first year they use LoSeasonique.

The following chart shows the chance of getting pregnant for women who use different methods of birth control. Each box on the chart contains a list of birth control methods that are similar in effectiveness. The most effective methods are at the top of the chart. The box on the bottom of the chart shows the chance of getting pregnant for women who do not use birth control and are trying to get pregnant.

Fewer than 1 pregnancy per 100 women in one year | Fewer Pregnancies | - Implants - Injections - Intrauterine devices - Sterilization
 |  | - Birth control pills - Skin patch - Vaginal ring with hormones
10-20 pregnancies per 100 women in one year |  | - Condoms - Diaphragm
10-20 pregnancies per 100 women in one year
10-20 pregnancies per 100 women in one year
10-20 pregnancies per 100 women in one year |  | - No sex during the most fertile days of the monthly cycle - Spermicide - Withdrawal
85 or more pregnancies per 100 women in one year | More Pregnancies | - No birth control

HOW DO I TAKE LoSeasonique?

1. Take one pill every day at the same time. If you miss pills you could get pregnant. This includes starting the pack late. The more pills you miss, the more likely you are to get pregnant.
2. Many women have spotting or light bleeding, or may feel sick to their stomach during the first few months of taking LoSeasonique. If you feel sick to your stomach, do not stop taking the pill. The problem will usually go away. If it doesn't go away, check with your healthcare provider.
3. Missing pills can also cause spotting or light bleeding, even when you take the missed pills later. On the days you take 2 pills to make up for missed pills, you could also feel a little sick to your stomach.
4. If you have trouble remembering to take LoSeasonique, talk to your healthcare provider about how to make pill-taking easier or about using another method of birth control.

Before you start taking LoSeasonique

1. Decide what time of day you want to take your pill. It is important to take it at about the same time every day.
2. Look at your Extended-Cycle Tablet Dispenser. Your Tablet Dispenser consists of 3 trays with cards that hold 91 individually sealed pills (a 13-week or 91-day cycle). The 91 pills consist of 84 orange and 7 yellow pills. Trays 1 and 2 each contain 28 orange pills (4 rows of 7 pills). Tray 3 contains 35 pills consisting of 28 orange pills (4 rows of 7 pills) and 7 yellow pills (1 row of 7 pills).
3. Also find:
  - Where on the first tray in the pack to start taking pills (upper left corner at the start arrow) and
  - In what order to take the pills (follow the weeks and arrow).
4. Be sure you have ready at all times another kind of birth control (such as condoms or spermicides), to use as a back-up in case you miss pills.

When to Start LoSeasonique

1. Take the first orange pill on the Sunday after your period starts, even if you are still bleeding. If your period begins on Sunday, start the first orange pill that same day.
2. Use another method of birth control (such as condoms or spermicides) as a back-up method if you have sex anytime from the Sunday you start your first orange pill until the next Sunday (first 7 days). If you have been using a different hormonal method of birth control (such as a different pill, the “patch,” or the “vaginal ring”), you need to use another method of birth control (such as condoms or spermicides) each time you have sex after stopping your old method of birth control until you have taken LoSeasonique for 7 days.

How to Take LoSeasonique

1. Take one pill at the same time every day until you have taken the last pill in the tablet dispenser.
  - Do not skip pills even if you are experiencing spotting or bleeding or feel sick to your stomach (nausea).
  - Do not skip pills even if you do not have sex very often.
2. When you finish a tablet dispenser
  - After taking the last yellow pill, start taking the first orange pill from a new Extended-Cycle Tablet Dispenser the very next day (this should be on a Sunday) regardless of when your period started.
3. If you miss your scheduled period when you are taking the yellow pills, contact your healthcare provider because you may be pregnant. If you are pregnant, you should stop taking LoSeasonique.

WHAT TO DO IF YOU MISS PILLS

If you MISS 1 orange pill:

1. Take it as soon as you remember. Take the next pill at your regular time. This means you may take 2 pills in 1 day.
2. You do not need to use a back-up birth control method if you have sex.

If you MISS 2 orange pills in a row:

1. Take 2 pills on the day you remember, and 2 pills the next day.
2. Then take 1 pill a day until you finish the pack.
3. You could become pregnant if you have sex in the 7 days after you miss two pills. You MUST use another birth control method (such as condoms or spermicide) as a back up for the 7 days after you restart your pills.

If you MISS 3 OR MORE orange pills in a row:

1. Do not take the missed pills. Keep taking 1 pill every day as indicated on the pack until you have completed all of the remaining pills in the pack. For example: If you resume taking the pill on Thursday, take the pill under “Thursday” and do not take the missed pills. You may experience bleeding during the week following the missed pills.
2. You could become pregnant if you have sex during the days of missed pills or during the first 7 days after restarting your pills.
3. You MUST use a non-hormonal birth control method (such as condoms or spermicide) as a back-up when you miss pills and for the first 7 days after you restart your pills. If you do not have your period when you are taking the yellow pills, call your healthcare provider because you may be pregnant.

If you MISS ANY of the 7 yellow pills:

1. Throw away the missed pills.
2. Keep taking the scheduled pills until the pack is finished.
3. You do not need a back-up method of birth control.

Finally, if you are still not sure what to do about the pills you have missed

1. Use a back-up method anytime you have sex.
2. Keep taking one pill each day until you contact your healthcare provider.

WHO SHOULD NOT TAKE LoSeasonique?

Your healthcare provider will not give you LoSeasonique if you have:

- Ever had breast cancer or any cancer that is sensitive to female hormones
- Liver disease, including liver tumors
- Ever had blood clots in your arms, legs, or lungs
- Ever had a stroke
- Ever had a heart attack
- Certain heart valve problems or heart rhythm abnormalities that can cause blood clots to form in the heart
- An inherited problem with your blood that makes it clot more than normal
- High blood pressure that medicine can't control
- Diabetes with kidney, eye, or blood vessel damage
- Certain kinds of severe migraine headaches with aura, numbness, weakness or changes in vision

Also, do not take birth control pills if you:

- Smoke and are over 35 years old
- Are pregnant

Birth control pills may not be a good choice for you if you have ever had jaundice (yellowing of the skin or eyes) caused by pregnancy.

WHAT ELSE SHOULD I KNOW ABOUT TAKING LoSeasonique?

Birth control pills do not protect you against any sexually transmitted disease, including HIV, the virus that causes AIDS.

Do not skip any pills, even if you do not have sex often.

Birth control pills should not be taken during pregnancy. However, birth control pills taken by accident during pregnancy are not known to cause birth defects.

If you are breastfeeding, consider another birth control method until you are ready to stop breastfeeding. Birth control pills that contain estrogen, like LoSeasonique, may decrease the amount of milk you make. A small amount of the pill's hormones pass into breast milk, but this has not caused harmful effects in breastfeeding infants.

Tell your health care provider about all medicines and herbal products that you take. Some medicines and herbal products may make birth control pills less effective, including:

- barbiturates
- bosentan
- carbamazepine
- felbamate
- griseofulvin
- oxcarbazepine
- phenytoin
- rifampin
- St. John’s wort
- topiramate

Consider using another birth control method when you take medicines that may make birth control pills less effective.

Birth control pills may interact with lamotrigine, an anticonvulsant used for epilepsy. This may increase the risk of seizures, so your physician may need to adjust the dose of lamotrigine.

If you have vomiting or diarrhea, your birth control pills may not work as well. Use another birth control method, like condoms or a spermicide, until you check with your health care provider.

WHAT ARE THE MOST SERIOUS RISKS OF TAKING BIRTH CONTROL PILLS?

Like pregnancy, birth control pills increase the risk of serious blood clots, especially in women who have other risk factors, such as smoking, obesity, or age > 35. It is possible to die from a problem caused by a blood clot, such as a heart attack or a stroke. Some examples of serious blood clots are blood clots in the:

- Legs (thrombophlebitis)
- Lungs (pulmonary embolus)
- Eyes (loss of eyesight)
- Heart (heart attack)
- Brain (stroke)

A few women who take birth control pills may get:

- High blood pressure
- Gallbladder problems
- Rare cancerous or noncancerous liver tumors

All of these events are uncommon in healthy women.

Call your health care provider right away if you have:

- Persistent leg pain
- Sudden shortness of breath
- Sudden blindness, partial or complete
- Severe pain in your chest
- Sudden, severe headache unlike your usual headaches
- Weakness or numbness in an arm or leg, or trouble speaking
- Yellowing of the skin or eyeballs

WHAT ARE COMMON SIDE EFFECTS OF BIRTH CONTROL PILLS?

The most common side effects of birth control pills are:

- Spotting or bleeding between menstrual periods
- Nausea
- Breast tenderness
- Headache

These side effects are usually mild and usually disappear with time.

Less common side effects are:

- Acne
- Less sexual desire
- Bloating or fluid retention
- Blotchy darkening of the skin, especially on the face
- High blood sugar, especially in women who already have diabetes
- High fat levels in the blood.
- Depression, especially if you have had depression in the past. Call your health care provider immediately if you have any thoughts of harming yourself.
- Problems tolerating contact lenses
- Weight changes

This is not a complete list of possible side effects. Talk to your health care provider if you develop any side effects that concern you.

No serious problems have been reported from a birth control pill overdose, even when accidentally taken by children.

DO BIRTH CONTROL PILLS CAUSE CANCER?

Birth control pills do not appear to cause breast cancer. However, if you have breast cancer now, or have had it in the past, do not use birth control pills because some breast cancers are sensitive to hormones.

Women who use birth control pills may have a slightly higher chance of getting cervical cancer. However, this may be due to other reasons such as having more sexual partners.

WHAT SHOULD I KNOW ABOUT MY PERIOD WHEN TAKING LoSeasonique?

When you take LoSeasonique, which has a 91-day extended dosing cycle, you should expect to have 4 scheduled periods per year (bleeding when you are taking the 7 yellow pills). Each period is likely to last about 2 to 3 days. However, you will probably have more bleeding or spotting between your scheduled periods than if you were using a birth control pill with a 28-day dosing cycle. This bleeding or spotting tends to decrease with time. Do not stop taking LoSeasonique because of this bleeding or spotting. If the spotting continues for more than 7 consecutive days or if the bleeding is heavy, call your healthcare provider.

WHAT IF I MISS MY SCHEDULED PERIOD WHEN TAKING LoSeasonique?

You should consider the possibility that you are pregnant if you miss your scheduled period (no bleeding on the days that you are taking yellow tablets). Since scheduled periods are less frequent when you are taking LoSeasonique, notify your healthcare provider that you have missed your period and that you are taking LoSeasonique. Also notify your healthcare provider if you have symptoms of pregnancy such as morning sickness or unusual breast tenderness. It is important that your healthcare provider evaluates you to determine if you are pregnant. Stop taking LoSeasonique if it is determined that you are pregnant.

WHAT IF I WANT TO BECOME PREGNANT?

You may stop taking the pill whenever you wish. Consider a visit with your health care provider for a pre-pregnancy checkup before you stop taking the pill.

Rx only

TEVA WOMEN’S HEALTH, INC.
Subsidiary of TEVA PHARMACEUTICALS USA, INC.
Sellersville, PA 18960

Iss. 6/2011

799-33-100090

Additional barcode labeling applied by:
Physicians Total Care, Inc.
Tulsa, Oklahoma 74146

PRINCIPAL DISPLAY PANEL

LoSEASONIQUE

levonorgestrel/ethinyl estradiol 0.1 mg/0.02 mg tablets

ethinyl estradiol 0.01 mg tablets

Rx only

Usual Dosage: One tablet daily for 91 consecutive days in the following order: 84 orange tablets followed by 7 yellow tablets as prescribed.

See enclosed package brochure.

Pharmacist: Dispense patient information with each prescription.

Contains 2 Extended-Cycle Tablet Dispensers, each containing 91 tablets: 84 orange tablets, each containing 0.1 mg levonorgestrel with 0.02 mg ethinyl estradiol, and 7 yellow tablets, each containing 0.01 mg ethinyl estradiol.

THIS PRODUCT (LIKE ALL ORAL CONTRACEPTIVES) IS INTENDED TO PREVENT PREGNANCY. IT DOES NOT PROTECT AGAINST HIV INFECTION (AIDS) AND OTHER SEXUALLY TRANSMITTED DISEASES.

Store at 20o to 25oC (68o to 77oF) [See USP Controlled Room Temperature].